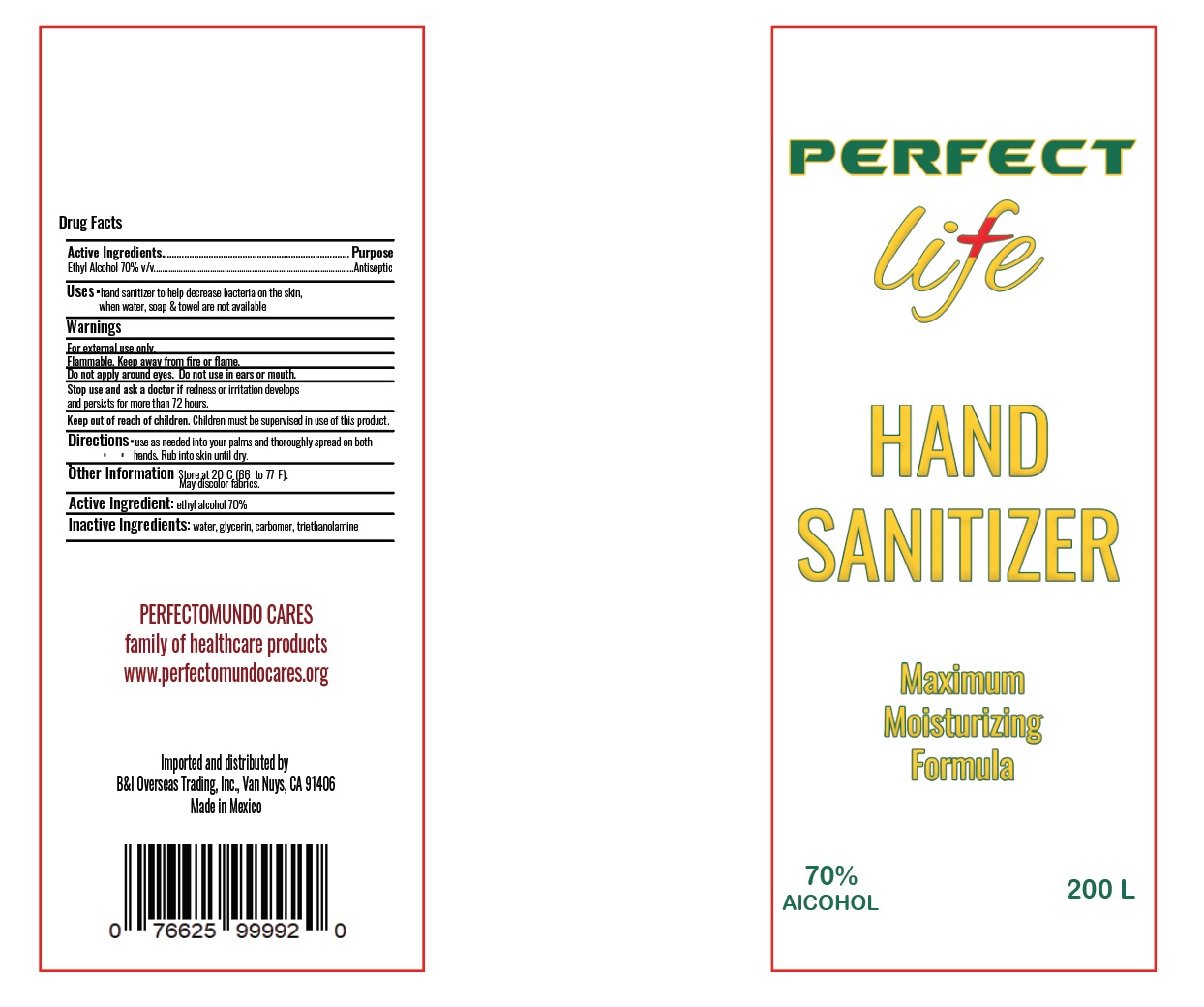 DRUG LABEL: PERFECT LIFE
NDC: 78501-2000 | Form: GEL
Manufacturer: COMERCIAL GOURA,S. DE R.L.
Category: otc | Type: HUMAN OTC DRUG LABEL
Date: 20200607

ACTIVE INGREDIENTS: ALCOHOL 0.7 L/1 L
INACTIVE INGREDIENTS: CARBOMER 940 0.002 L/1 L; GLYCERIN 0.0375 L/1 L; TRIETHANOLAMINE CAPROYL GLUTAMATE 0.002 L/1 L; WATER 0.2585 L/1 L

HAND SANITIZER GEL DRUM

DOSAGE AND ADMINISTRATION

Directions

Place enough product on hands to cover all surfaces. Rub hands together until dry.

INACTIVE INGREDIENTS

Inactive ingredients Water (Aqua), Glycerin, Carbomer, Triethanolamine

DIRECTIONS

Place enough product on hands to cover all surfaces. Rub hands together until dry.

When using this product keep out of eyes, ears, and mouth. In case of contact with eyes, rinse eyes thoroughly with water.

Keep out of reach of children. If swallowed, get medical help or contact a Poison Control Center right away.

ACTIVE INGREDIENT

Active ingredient. Ethyl Alcohol 70% v/v

PURPOSE

Purpose Antmicrobial

WARNINGS AND PRECAUTIONS SECTION

Warnings

For external use only. Flammable. Keep away from heat or flame

Children under 6 years of age should be supervised when using.

Other information

Store below 110°F (43°C)

WARNINGS

For external use only. Flammable. Keep away from heat or flame

Stop use and ask a doctor if irritation or rash occurs. These may be signs of a serious condition.